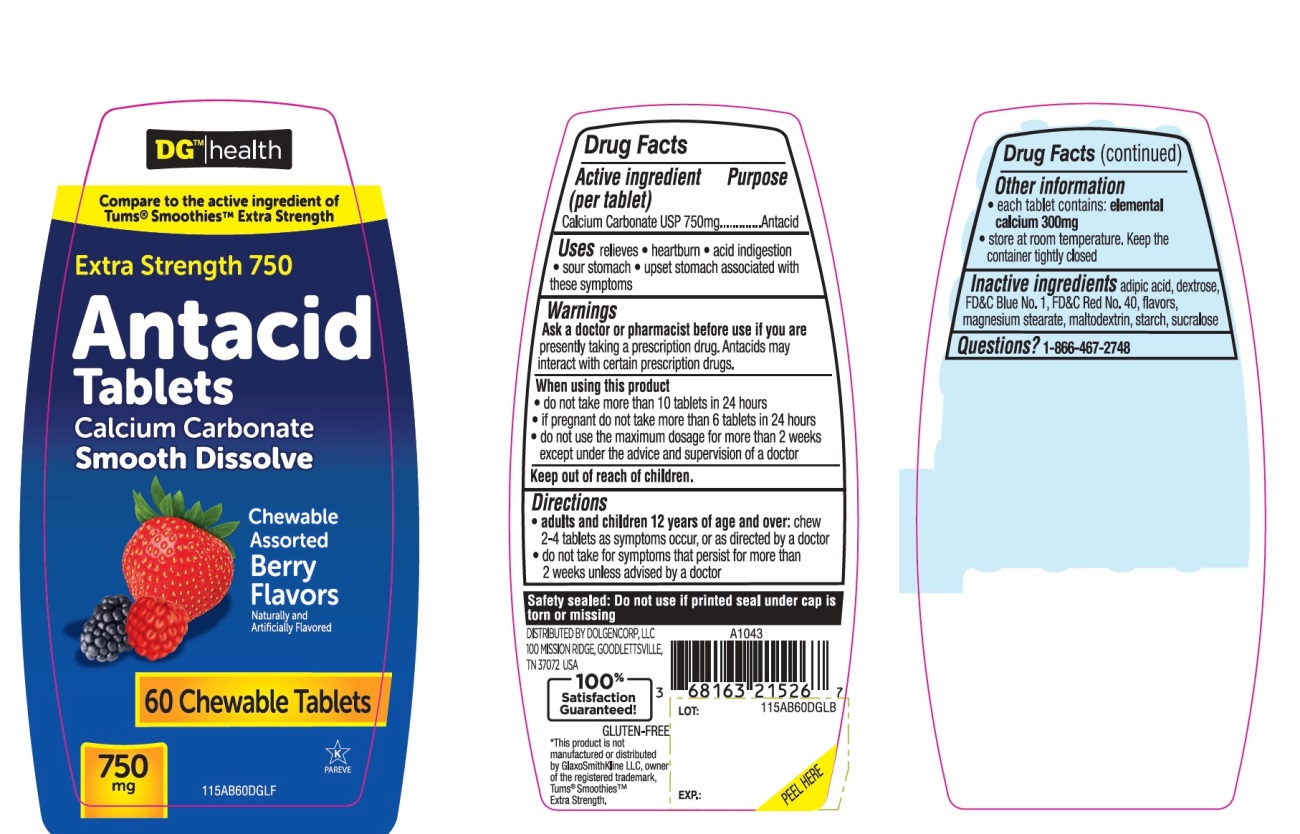 DRUG LABEL: DG health Extra Strength

NDC: 55910-115 | Form: TABLET, CHEWABLE
Manufacturer: DOLGENCORP, LLC
Category: otc | Type: HUMAN OTC DRUG LABEL
Date: 20250822

ACTIVE INGREDIENTS: CALCIUM CARBONATE 750 mg/1 1
INACTIVE INGREDIENTS: ADIPIC ACID; DEXTROSE, UNSPECIFIED FORM; FD&C BLUE NO. 1; FD&C RED NO. 40; MAGNESIUM STEARATE; MALTODEXTRIN; STARCH, CORN; SUCRALOSE

Extra Strength Antacid Assorted Berries 60 Chewable Tablets

Active ingredient (per tablet)

Calcium Carbonate USP 750 mg

Purpose

Antacid

Uses

relieves

- heartburn
- acid indigestion
- sour stomach
- upset stomach associated with these symptoms

Warnings

Ask a doctor or pharmacist before use if you arepresently taking a prescription drug. Antacids may interact with certain prescription drugs.

When using this product

- do not take more than 10 tablets in 24 hours
- if pregnant do not take more than 6 tablets in 24 hours
- do not use the maximum dosage for more than 2 weeks except under the advice and supervision of a doctor

Directions

- adults and children 12 years of age and over:chew 2-4 tablets as symptoms occur, or as directed by a doctor
- do not take for symptoms that persist for more than 2 weeks unless advised by a doctor

Other information

- each tablet contains: elemental calcium 300mg
- store at room temperature. Keep the container tightly closed

Inactive ingredients

adipic acid, dextrose, FD&C Blue No. 1, FD&C Red No. 40, flavors, magnesium stearate, maltodextrin, starch, sucralose.

Questions?

1-866-467-2748

DO NOT USE IF PRINTED SEAL UNDER CAP IS TORN OR MISSING

Package/Label Principal Display Panel

DG™ health

NDC# 55910-115-60

Compare to the active ingredient Tums® Smoothies™ Extra Strength

Extra Strength 750

Antacid Tablets

Calcium Carbonate

Smooth Dissolve

Chewable Assorted Berry Flavors

Naturally and Artificially Flavored

750 mg

60 Chewable Tablets

K PAREVE

GLUTEN- FREE

100% Satisfaction Guaranteed!

DISTRIBUTED BY DOLGENCORP, LLC

100 MISSION RIDGE, GOODLETTISVILLE,

TN 37072, USA

*This product is not manufactured or distributed by GlaxoSmithKline, owner of the registered trademark, Tums® Smoothies™ Extra Strength.